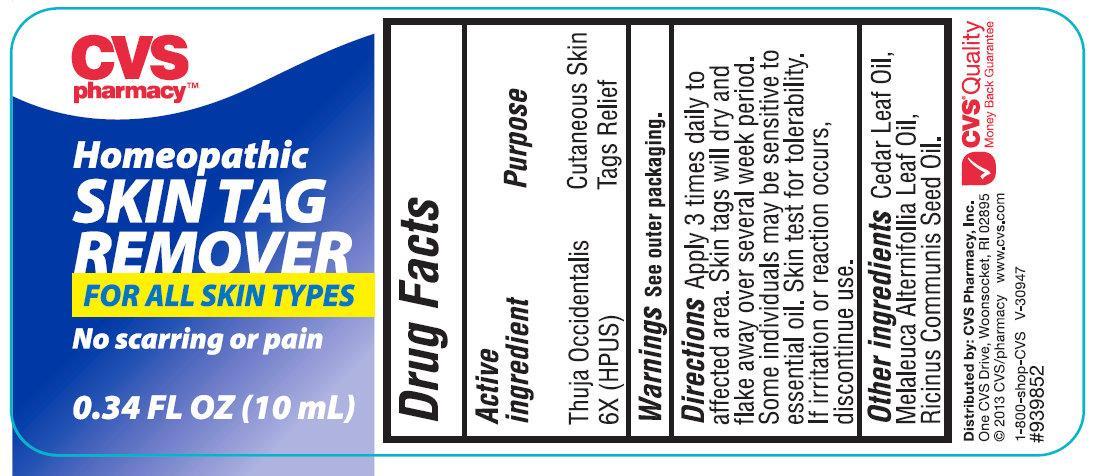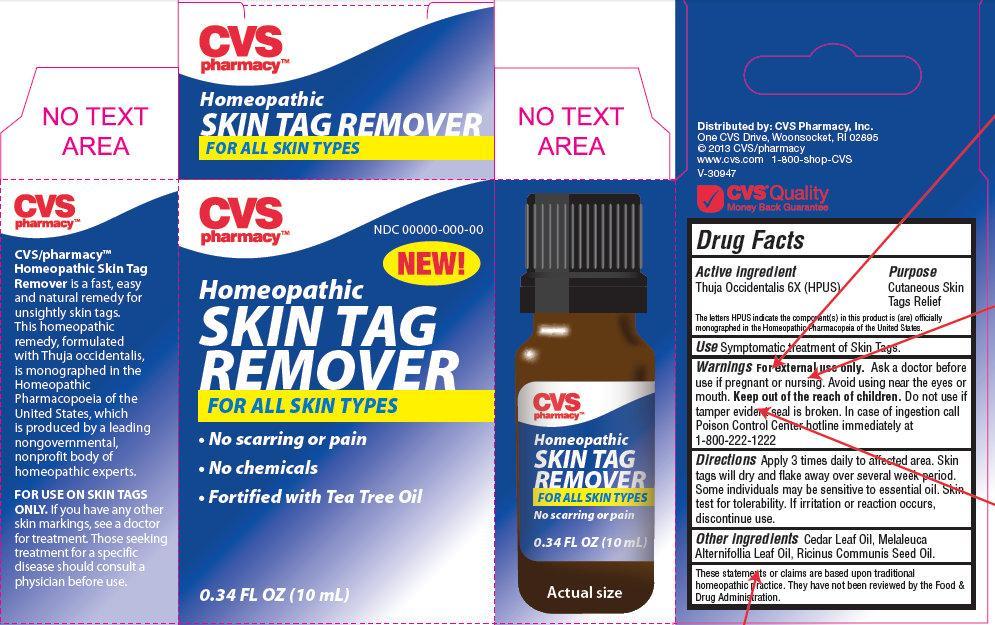 DRUG LABEL: CVS Homeopathic SKIN TAG REMOVER
NDC: 59779-983 | Form: LIQUID
Manufacturer: CVS Pharmacy, Inc
Category: homeopathic | Type: HUMAN OTC DRUG LABEL
Date: 20190110

ACTIVE INGREDIENTS: THUJA OCCIDENTALIS LEAFY TWIG 6 [hp_X]/10 mL
INACTIVE INGREDIENTS: CEDAR LEAF OIL; MELALEUCA ALTERNIFOLIA LEAF; CASTOR OIL

CVS Homeopathic SKIN TAG REMOVER

Active ingredient

Thuja Occidentalis 6X (HPUS)

The letters HPUS indicate the component(s) in this product is (are) officially monographed in the Homeopathic Pharmacopeia of the United States.

Purpose

Cutaneous Skin Tags Relief

Use

Symptomatic treatment of Skin Tags.

Warnings

For external use only.

Ask a doctor before use

if pregnant or nursing.

Avoid using

near the eyes or mouth.

Do not use

if tamper evident seal is broken. In case of ingestion call Poison Control Center hotline immediately at 1-800-222-1222

Directions

- Apply 3 times daily to affected area. Skin tags will dry and flake away over several week period. Some individuals may be sensitive to essential oil. Skin test for tolerability. If irritation or reaction occurs, discontinue use.

Other ingredients

Cedar Leaf Oil, Melaleuca Alternifollia Leaf Oil, Ricinus Communis Seed Oil.